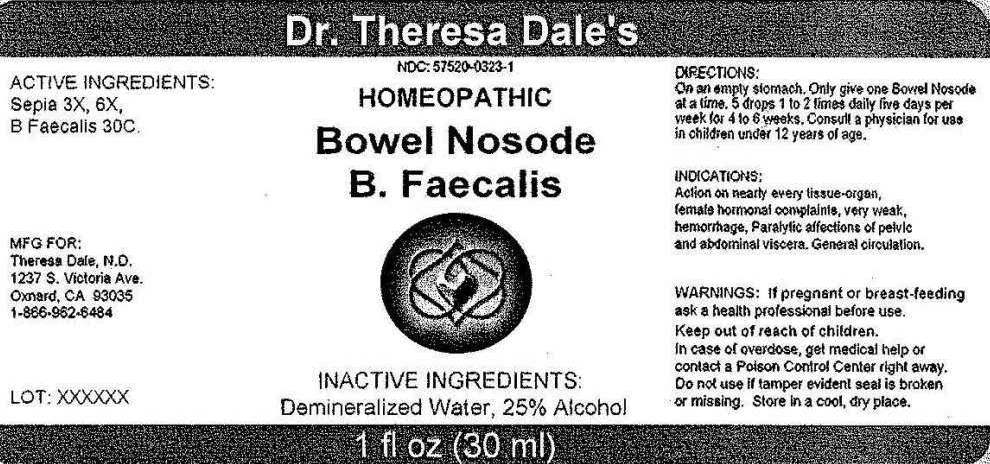 DRUG LABEL: Bowel Nosode B Faecalis
NDC: 57520-0323 | Form: LIQUID
Manufacturer: Apotheca Company
Category: homeopathic | Type: HUMAN OTC DRUG LABEL
Date: 20120118

ACTIVE INGREDIENTS: SEPIA OFFICINALIS JUICE 3 [hp_X]/1 mL; ALCALIGENES FAECALIS 30 [hp_C]/1 mL
INACTIVE INGREDIENTS: WATER; ALCOHOL

Bowel Nosode B Faecalis

ACTIVE INGREDIENTS: Sepia 3X, 6X, B. Faecalis 30C.

PURPOSE

INDICATIONS: Action on nearly every tissue-organ, female hormonal complaints, very weak hemorrhage, paralytic affections of pelvic and abdominal viscera, general circulation.

WARNINGS

WARNINGS: If pregnant or breast-feeding, ask a health professional before use.

Keep out of reach of children.

In case of overdose, get medical help or contact a Poison Control Center right away.

Do not use if tamper evident seal is broken or missing. Store in a cool, dry place.

DOSAGE AND ADMINISTRATION

DIRECTIONS: On an empty stomach. Only give one Bowel Nosode at a time. 5 drops 1 to 2 times daily five days per week for 4 to 6 weeks. Consult a physician for use in children under 12 years of age.

INACTIVE INGREDIENTS: Demineralized water, 25% Alcohol

KEEP OUT OF REACH OF CHILDREN. In case of overdose, get medical help or contact a Poison Control Center right away.

INDICATIONS AND USAGE

INDICATIONS: Action on nearly every tissue-organ, female hormonal complaints, very weak hemorrhage, paralytic affections of pelvic and abdominal viscera, general circulation.

QUESTIONS

MFG. FOR:

Theresa Dale N.D.

1237 S Victoria Ave.

Oxnard, CA 93035

1-866-962-6484

PACKAGE LABEL

Dr. Theresa Dale's

NDC 57520-0323-1

HOMEOPATHIC

Bowel Nosode B. Faecalis

1 fl oz (30 ml)